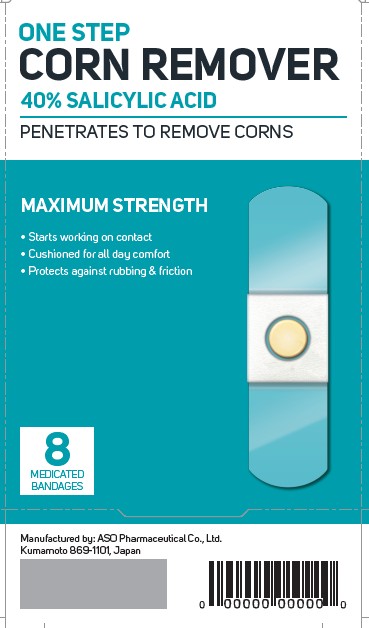 DRUG LABEL: Salicylic Acid 40% / Corn Remover
NDC: 51511-599 | Form: PLASTER
Manufacturer: ASO Pharmaceutical Co.,ltd.
Category: otc | Type: HUMAN OTC DRUG LABEL
Date: 20250509

ACTIVE INGREDIENTS: SALICYLIC ACID 0.4 g/1 g
INACTIVE INGREDIENTS: GLYCERYL ROSINATE; POLYBUTENE (1400 MW); LANOLIN; NATURAL LATEX RUBBER

Corn Remover

Active ingredient

Salicylic acid 40%

Corn Remover

Wart remover

Warnings

For external use only

Do not use

- if you are a diabetic
- if you have poor blood circulation
- on irritated skin or any area that is infected or reddened

Stop use and ask a doctor if

discomfort persists

Keep out of reach of children

If swallowed, get medical help or contact a Poison Control Center (1-800-222-1222) right away

Directions

- wash affected area and dry thoroughly
- apply medicated bandage
- after 48 hours, remove medicated bandage

DOSAGE AND ADMINISTRATION

- repeat procedure every 48 hours as needed for up to 14 days (until corn is removed)
- may soak in warm water for 5 minutes to assist in removal

Other information

- store at room temperature
- avoid excessive heat 27C (99F)

Inactive ingredients

lanolin, polybutene, rosin ester, rubber

Principal Display Panel

ONE STEP

CORN REMOVER

40% SALICYLIC ACID

PENETRATES TO REMOVE CORNS

MAXIMUM STRENGTH

- Starts working on contact
- Cushioned for all day comfort
- Protects against rubbing & friction